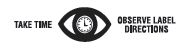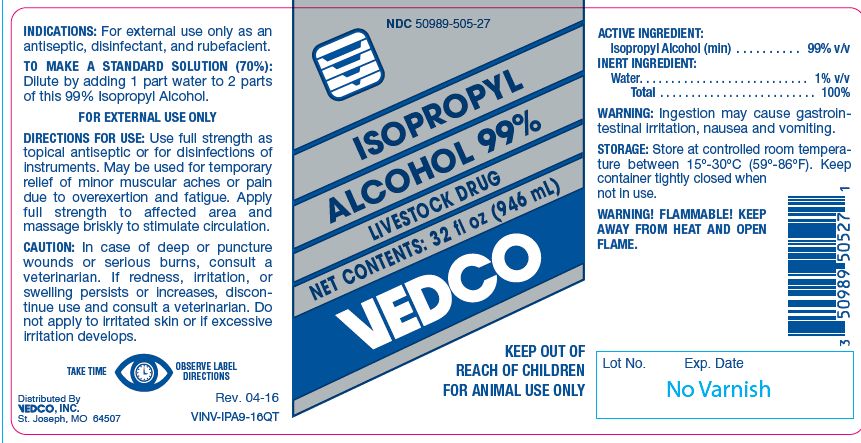 DRUG LABEL: Isopropyl Alcohol
NDC: 50989-505 | Form: LIQUID
Manufacturer: Vedco, Inc.
Category: animal | Type: OTC ANIMAL DRUG LABEL
Date: 20241029

ACTIVE INGREDIENTS: ISOPROPYL ALCOHOL 785 g/1 L

ISOPROPYL ALCOHOL 99%

KEEP OUT OF REACH OF CHILDREN
FOR ANIMAL USE ONLY

INDICATIONS:

For external use only as an antiseptic, disinfectant, and rubefacient.

TO MAKE A STANDARD SOLUTION (70%):

Dilute by adding 1 part water to 2 parts of this 99% Isopropyl Alcohol.
FOR EXTERNAL USE ONLY

DIRECTIONS FOR USE:

Use full strength as topical antiseptic or for disinfections of instruments. May be used for temporary relief of minor muscular aches or pain due to overexertion and fatigue. Apply full strength to affected area and massage briskly to stimulate circulation.

CAUTION:

In case of deep or puncture wounds or serious burns, consult a veterinarian. If redness, irritation, or swelling persists or increases, discontinue use and consult a veterinarian. Do not apply to irritated skin or if excessive irritation develops.

ACTIVE INGREDIENT:

Isopropyl Alcohol (min) . . . . . . . . . . 99% v/v

INERT INGREDIENT:

Water. . . . . . . . . . . . . . . . . . . . . . . . . . . 1% v/v
Total . . . . . . . . . . . . . . . . . . . . . . . . . 100%

WARNING:

Ingestion may cause gastrointestinal irritation, nausea and vomiting.

STORAGE:

Store at controlled room temperature between 15º-30ºC (59º-86ºF). Keep container tightly closed when not in use.

WARNINGS AND PRECAUTIONS

WARNING! FLAMMABLE! KEEP AWAY FROM HEAT AND OPEN FLAME.

Net Contents:

32 fl oz (946 mL) VINV-IPA9-16QT

INFORMATION FOR OWNERS/CAREGIVERS

Distributed By
VEDCO, INC.
St. Joseph, MO 64507